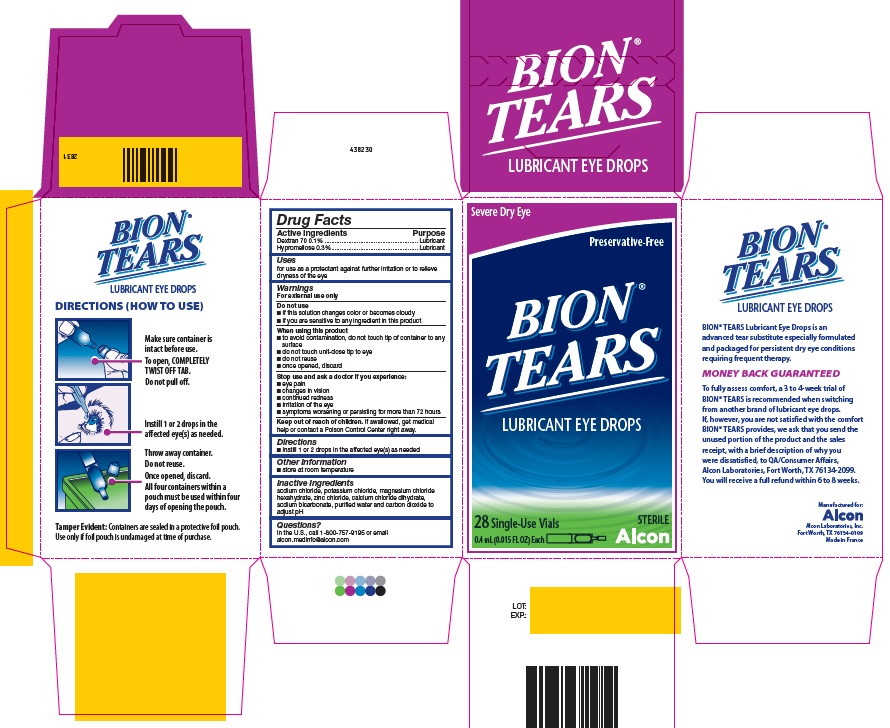 DRUG LABEL: BION TEARS
NDC: 0065-9305 | Form: SOLUTION/ DROPS
Manufacturer: Alcon Laboratories, Inc.
Category: otc | Type: HUMAN OTC DRUG LABEL
Date: 20231214

ACTIVE INGREDIENTS: Dextran 70 1 mg/1 mL; Hypromellose 2910 (4000 Mpa.s) 3 mg/1 mL
INACTIVE INGREDIENTS: Sodium Chloride; Potassium Chloride; Magnesium Chloride; Zinc Chloride; Calcium Chloride; Sodium Bicarbonate; Water; Carbon Dioxide

Drug Facts

ACTIVE INGREDIENT

Active Ingredients | Purpose
Dextran 70 0.1% | Lubricant
Hypromellose 2910 0.3% | Lubricant

Uses

- For use as a protectant against further irritation or to relieve dryness of the eye.

Warnings

For external use only

Do not use

- if this solution changes color or becomes cloudy.
- if you are sensitive to any ingredient in this product.

When using this product

- To avoid contamination, do not touch tip of container to any surface.
- Do not touch unit-dose tip to eye.
- Do not reuse.
- Once opened, discard.

Stop use and ask a doctor if you experience

- eye pain
- changes in vision
- continued redness
- irritation of the eye
- symptoms worsening or persisting for more than 72 hours

Keep out of reach of children. If swallowed, get medical help or contact a Poison Control Center right away.

Directions

- Instill 1 or 2 drops in the affected eye(s) as needed.

Other Information

Store at room temperature.

Inactive Ingredients

Sodium chloride, potassium chloride, magnesium chloride hexahydrate, zinc chloride, calcium chloride dihydrate, sodium bicarbonate, purified water and carbon dioxide to adjust pH.

Questions?

In the U.S. call 1-800-757-9195 or email
alcon.medinfo@alcon.com

PRINCIPAL DISPLAY PANEL

Severe Dry Eye
Preservative-Free
BION® TEARS
LUBRICANT EYE DROPS
28 Single-Use Vials
0.4 ml (0.015 FL OZ) Each
STERILE
Alcon
DIRECTIONS (HOW TO USE)
Make sure container is intact before use.
To open, COMPLETELY TWIST OFF TAB.
Do not pull off.
Instill 1 or 2 drops in the affected eye(s) as needed.
Throw away container.
Do not reuse.
Once opened, discard.
All four containers within a pouch must be used within four days of opening the pouch.
Tamper Evident: Containers are sealed in a protective foil pouch. Use only if foil pouch is undamaged at time of purchase.
BION® TEARS Lubricant Eye Drops is an advanced tear substitute especially formulated and packaged for persistent dry eye conditions requiring frequent therapy.
MONEY BACK GUARANTEED
To fully assess comfort, a 3 to 4-week trial of BION® TEARS is recommended when switching from another brand of lubricant eye drops. If, however, you are not satisfied with the comfort BION® TEARS provides, we ask that you send the unused portion of the product and the sales receipt, with a brief description of why you were dissatisfied, to QA/Consumer Affairs, Alcon Laboratories, Fort Worth, TX 76134-2099. You will receive a full refund within 6 to 8 weeks.
Manufactured for:
Alcon
Alcon Laboratories, Inc.
Fort Worth, TX 76134-0109
Made in France
438230